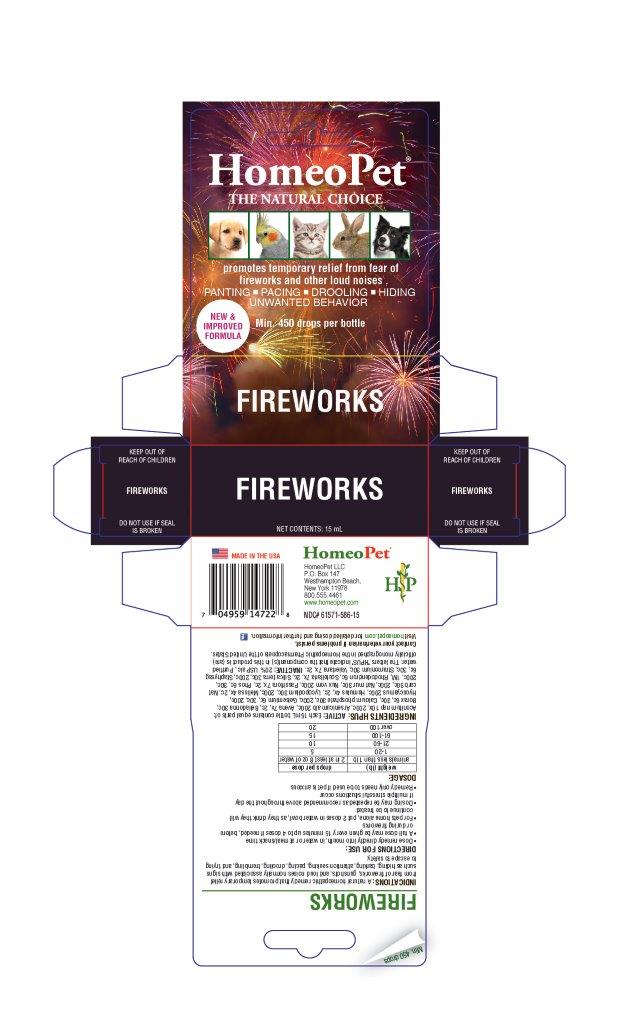 DRUG LABEL: Fireworks
NDC: 61571-586 | Form: LIQUID
Manufacturer: HomeoPet, LLC
Category: homeopathic | Type: OTC ANIMAL DRUG LABEL
Date: 20201030

ACTIVE INGREDIENTS: ACONITUM NAPELLUS 10 [hp_X]/15 mL; ARSENIC TRIOXIDE 200 [hp_C]/15 mL; AVENA SATIVA FLOWERING TOP 7 [hp_X]/15 mL; ATROPA BELLADONNA 30 [hp_C]/15 mL; SODIUM BORATE 6 [hp_C]/15 mL; TRIBASIC CALCIUM PHOSPHATE 30 [hp_C]/15 mL; GELSEMIUM SEMPERVIRENS ROOT 6 [hp_C]/15 mL; HYOSCYAMUS NIGER 200 [hp_C]/15 mL; HOPS 4 [hp_X]/15 mL; LYCOPODIUM CLAVATUM SPORE 30 [hp_C]/15 mL; MELISSA OFFICINALIS 4 [hp_X]/15 mL; SODIUM CARBONATE 30 [hp_C]/15 mL; SODIUM CHLORIDE 30 [hp_C]/15 mL; STRYCHNOS NUX-VOMICA SEED 200 [hp_C]/15 mL; PASSIFLORA INCARNATA FLOWERING TOP 7 [hp_X]/15 mL; PHOSPHORUS 6 [hp_C]/15 mL; RHODODENDRON AUREUM LEAF 6 [hp_C]/15 mL; SCUTELLARIA LATERIFLORA 7 [hp_X]/15 mL; SILICON DIOXIDE 30 [hp_C]/15 mL; DELPHINIUM STAPHISAGRIA SEED 6 [hp_C]/15 mL; DATURA STRAMONIUM 30 [hp_C]/15 mL; VALERIAN 7 [hp_X]/15 mL
INACTIVE INGREDIENTS: ALCOHOL; WATER

Fireworks

Fireworks

Promotes temporary relief from fear of fireworks and other loud noises

PANTING-PACING-DROOLING-HIDING

UNWANTED BEHAVIOR

Directions for Use and Dosage Information

- Dose remedy directly into mouth, in water or at meal/snack time
- A full dose may be given every 15 minutes up to 4 doses if needed, before or during fireworks
- For pets home alone, put 2 doses in water bowl, as they drink they will continue to be treated
- Dosing may be repeated as recommended above throughout the day if multiple stressful situations occur
- Remedy only needs to be used if pet is anxious
  weight (lb) | drops per dose
  animals less than 1 lb | 2 in at least 8 oz of water
  1-20 | 5
  21-60 | 10
  61-100 | 15
  over 100 | 20

Contact Veterinarian

Contact Veterinarian if problems persist.

Visit homeopet.com for detailed dosing and further information.

Ingredients HPUS:Active

Aconitum nap 10x, 200c, Arsenicum alb 200c, Avena 7x, 2c, Belladonna 30c, Borax 6c, 30c, Calcium phosphate 30c, 200c, Gelsemium 6c, 30c, 200c, Hyoscyamus 200c, Humulus 4x, 2c, Lycopodium 30c, 200c, Melissa 4x, 2c, Nat carb 30c, 200c, Nat mur 30c, Nux vom 200c, Passiflora 7x, 2c, Phos 6c, 30c, 200c, 1M, Rhododendron 6c, Scutellaria 7x, 2c, Silica terra 30c, 200c, Staphysag 6c, 30c, Stramonium 30c, Valeriana 7x, 2c.

Inactive Ingredients

USP Alcohol, Purified Water

Indications

A natural homeopathic remedy that promotes temporary relief from fear of fireworks, gunshots, and loud noises normally associated with signs such as hiding, barking, attention seeking, pacing, drooling, trembling and trying to escape to safety.